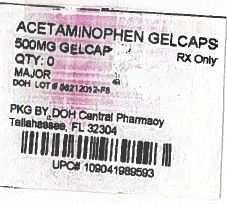 DRUG LABEL: MAPAP
NDC: 53808-0822 | Form: CAPSULE
Manufacturer: State of Florida DOH Central Pharmacy
Category: otc | Type: HUMAN OTC DRUG LABEL
Date: 20130808

ACTIVE INGREDIENTS: ACETAMINOPHEN 500 mg/1 1
INACTIVE INGREDIENTS: FD&C BLUE NO. 1; FD&C RED NO. 40; GELATIN; POVIDONE K30; STARCH, CORN; SODIUM STARCH GLYCOLATE TYPE A POTATO; STEARIC ACID; TITANIUM DIOXIDE

Extra Strength APAP Capsules

Drug Facts

Active Ingredient

(in each capsule)
Acetaminophen 500 mg

Purposes

Analgesic, Antipyretic

Uses

- temporarily relieves minor aches and pains due to
- the common cold
- headache
- toothache
- muscular aches
- backache
- minor pain of arthritis
- premenstrual and menstrual cramps
- temporarily reduces fever

Warnings

Liver warning: This product contains acetaminophen. Severe liver damage may occur if you take

- more than 8 capsules in 24 hours, which is the maximum daily amount
- with other drugs containing acetaminophen
- 3 or more alcoholic drinks every day while using this product

Do not use

- with any other drugs containing acetaminophen (prescription or nonprescription). If you are not sure whether a drug contains acetaminophen, ask a doctor or pharmacist.
- if you are allergic to acetaminophen or any of the inactive ingredients in this product

Ask a doctor before use if you have

liver disease

Ask a doctor before use if you are

taking the blood thinning drug warfarin

Stop use and ask a doctor if

- new symptoms occur
- redness or swelling is present
- pain gets worse or lasts for more than 10 days
- fever gets worse or lasts more than 3 days

These could be signs of a serious condition.

If pregnant or breast-feeding,

ask a health professional before use.

Keep out of reach of children.

Overdose warning Taking more than the recommended dose (overdose) may cause liver damage. In case of In case of overdose, get medical help or contact Poison Control Center right away. (1-800-222-1222) Quick medical attention is critical for adults as well as children even if you do not notice any signs or symptoms.

Directions

adults and children 12 years of age and over | take 2 capsules every 4 hour to 6 hours, not to exceed 8 capsules in 24 hours. Do not take for more than 10 days unless directed by a doctor.
children under 12 years of age | Do not use Extra Strength product in children 12 years of age; this will provide more than the recommended dose (overdose) of pain reliever and could cause liver damage.

DO NOT EXCEED RECOMMENDED DOSE

Other information

- store at room temperature, USP
- use by expiration date on pckage
- do not use if capsule band or imprinted safety seal under cap is broken or missing
- side effects occur
- You may report side effects at 1-800-616-2471 (Toll Free)

Inactive Ingredients

FD&C Blue #1, FD&C Red #40, Gelatin, Polyvinylpyrrolidone, Pregelatinized Starch, Sodium Starch Glycolate, Stearic Acid and Titanium Dioxide.

*Major Extra Strength Mapap is not manufactured or distributed by McNeil Consumer Healthcare, owner of the registered trademark Extra Strength Tylenol®.

Distributed by:
MAJOR PHARMACEUTICALS
Livonia, MI 48150 USA

This Product was Repackaged By:

State of Florida DOH Central Pharmacy
104-2 Hamilton Park Drive
Tallahassee, FL 32304
United States

They are supplied by State of Florida DOH Central Pharmacy as follows:

NDC | Strength | Quantity/Form | Color | Source Prod. Code
53808-0822-1 | 500 mg | 30 Capsules in a Blister Pack | RED | 0904-1987